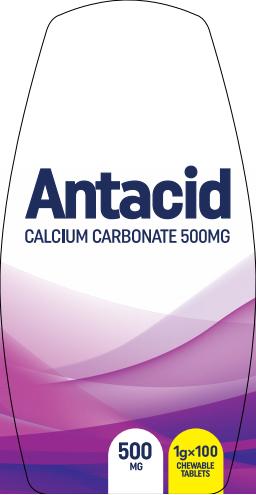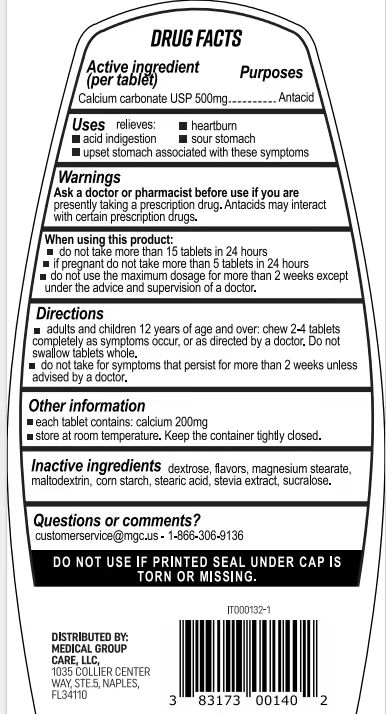 DRUG LABEL: Antacid
NDC: 83698-002 | Form: TABLET
Manufacturer: Xiamen Kang Zhongyuan Biotechnology Co., Ltd.
Category: otc | Type: HUMAN OTC DRUG LABEL
Date: 20251226

ACTIVE INGREDIENTS: CALCIUM CARBONATE 500 mg/1 g
INACTIVE INGREDIENTS: ICODEXTRIN; MAGNESIUM STEARATE; ANHYDROUS DEXTROSE

83698-002

Active Ingredient

Calcium carbonate 500mg

Purpose

Antacid

Use

1.heartourn

2.acid indigestion

3.sour stomach

4.upset stomach associated with these symptoms

Warnings

Ask a doctor or pharmacist before use if you are presently taking a prescription drug. Antacids may interact with certain prescription drugs.

Do not use

IF PRINTED SEAL UNDER CAP IS TORN OR MISSING.

When Using

1.do not take more than 15 tablets in 24 hours.

2.if pregnant do not take more than 5 tablets in 24 hours.
3.do not use the maximum dosage for more than 2 weeks except under the advice and supervision of a doctor.

Keep Oot Of Reach Of Children

If a child ingests it, call emergency services immediately.

Directions

1.adults and children 12 years of age and over: chew 2-4 tablets completely as symptoms occur, or as directed by a doctor. Do not swallow tablets whole.
2.do not take for symptoms that persist for more than 2 weeks unless advised by a doctor.

Other information

1.each tablet contains: calcium 200mg
2.store at room temperature. Keep the container tighty closed.

Inactive ingredients

medicinal dextrin, anhydrous glucose, magnesium stearate.

Questions

0086-0592--7290587